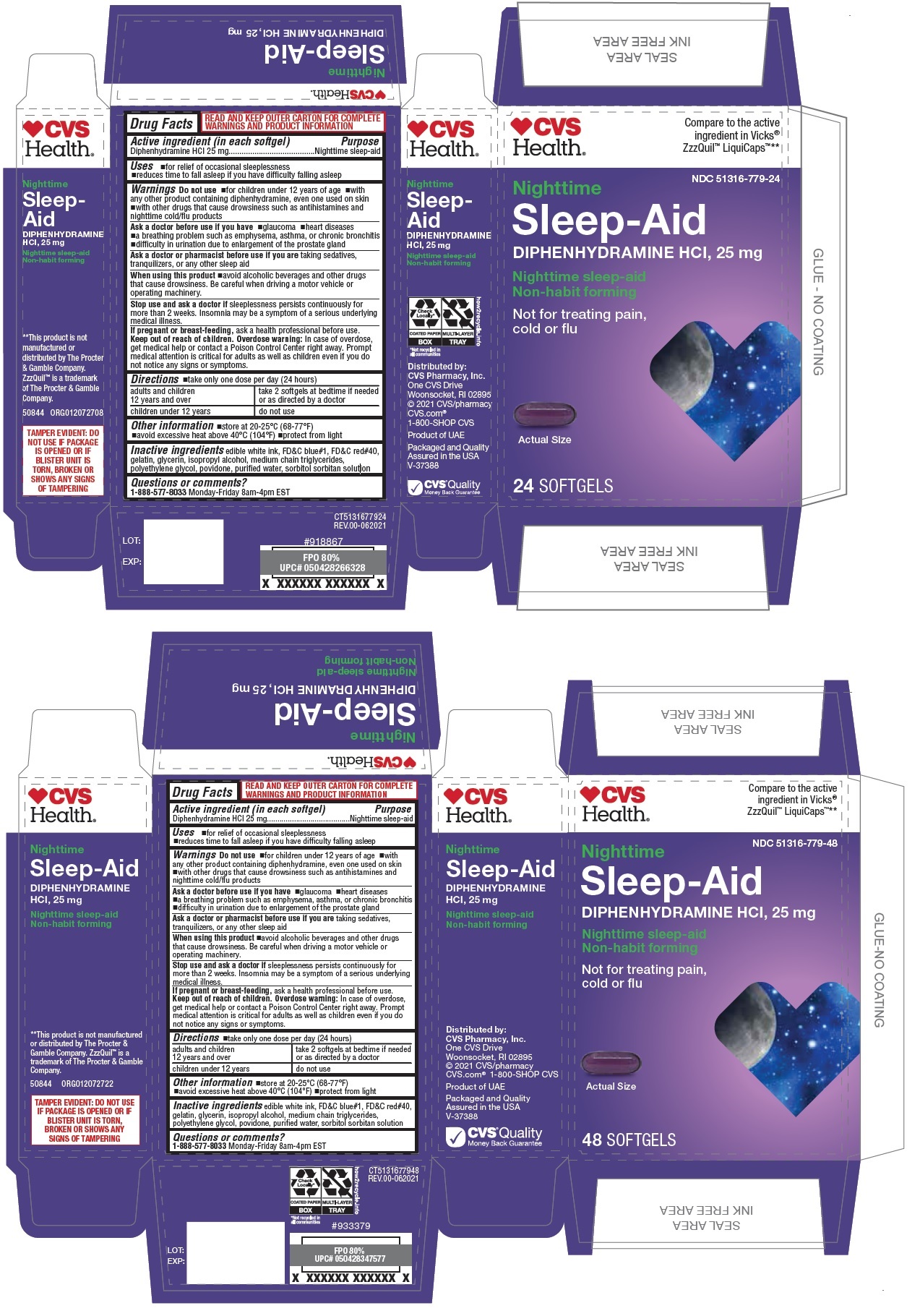 DRUG LABEL: Nighttime Sleep-Aid Softgel
NDC: 51316-779 | Form: CAPSULE, LIQUID FILLED
Manufacturer: CVS PHARMACY, INC
Category: otc | Type: HUMAN OTC DRUG LABEL
Date: 20250101

ACTIVE INGREDIENTS: DIPHENHYDRAMINE HYDROCHLORIDE 25 mg/1 1
INACTIVE INGREDIENTS: FD&C BLUE NO. 1; FD&C RED NO. 40; GELATIN, UNSPECIFIED; GLYCERIN; ISOPROPYL ALCOHOL; MEDIUM-CHAIN TRIGLYCERIDES; POLYETHYLENE GLYCOL, UNSPECIFIED; POVIDONE, UNSPECIFIED; WATER; SORBITOL; SORBITAN

Nighttime Sleep-Aid Softgel

Active ingredient (in each softgel)

Diphenhydramine HCl 25 mg

Purpose

Nighttime sleep-aid

Uses

• for relief of occasional sleeplessness
• reduces time to fall asleep if you have difficulty falling asleep

Warnings

Do not use • for children under 12 years of age • with any other product containing diphenhydramine, even one used on skin • with other drugs that cause drowsiness such as antihistamines and nighttime cold/flu products

Ask a doctor before use if you have • glaucoma • heart diseases • a breathing problem such as emphysema, asthma, or chronic bronchitis • difficulty in urination due to enlargement of the prostate gland

Ask a doctor or pharmacist before use if you are taking sedatives, tranquilizers, or any other sleep aid

When using this product avoid alcoholic beverages and other drugs that cause drowsiness. Be careful when driving a motor vehicle or operating machinery

Stop use and ask a doctor if sleeplessness persists continuously for more than 2 weeks. Insomnia may be a symptom of a serious underlying medical illness.

If pregnant or breast-feeding, ask a health professional before use.

Keep out of reach of children. Overdose warning: In case of overdose, get medical help or contact a Poison Control Center right away. Prompt medical attention is critical for adults as well as children even if you do not notice any signs or symptoms.

Directions

• take only one dose per day (24 hours)
• adults and children 12 years and over: take 2 softgels at bedtime if needed or as directed by a doctor
• children under 12 years: do not use

Other information

• store at 20-25°C (68-77°F)

Inactive ingredients

FD&C blue#1, FD&C red#40, gelatin, glycerin, isopropyl alcohol, medium chain triglycerides, polyethylene glycol, povidone, purified water, sorbitol sorbitan solution, white ink

Questions or comments?

1-888-577-8033 Monday-Friday 9am-4:30pm EST

Compare to the active ingredient in Vicks® ZzzQuil™ NIGHTTIME SLEEP-AID LiquidCaps™**

Non-habit forming

Not for treating pain, cold or flu

**This product is not manufactured or distributed by The Proctor & Gamble Company, owner of the registered trademark VICKS® ZzzQuil™ NIGHTTIME SLEEP-AID LiquiCaps™.

TAMPER EVIDENT: DO NOT USE IF BLISTER UNIT IS TORN, BROKEN OR SHOWS SIGNS OF TAMPERING

READ AND KEEP OUTER CARTON FOR COMPLETE WARNINGS AND PRODUCT INFORMATION

Product of UAE

Packaged and Quality Assured in the USA

Distributed by:
CVS Pharmacy, Inc.
One CVS Drive
Woonsocket, RI 02895
© 2021 CVS/pharmacy
CVS.com®
1-800-SHOP CVS